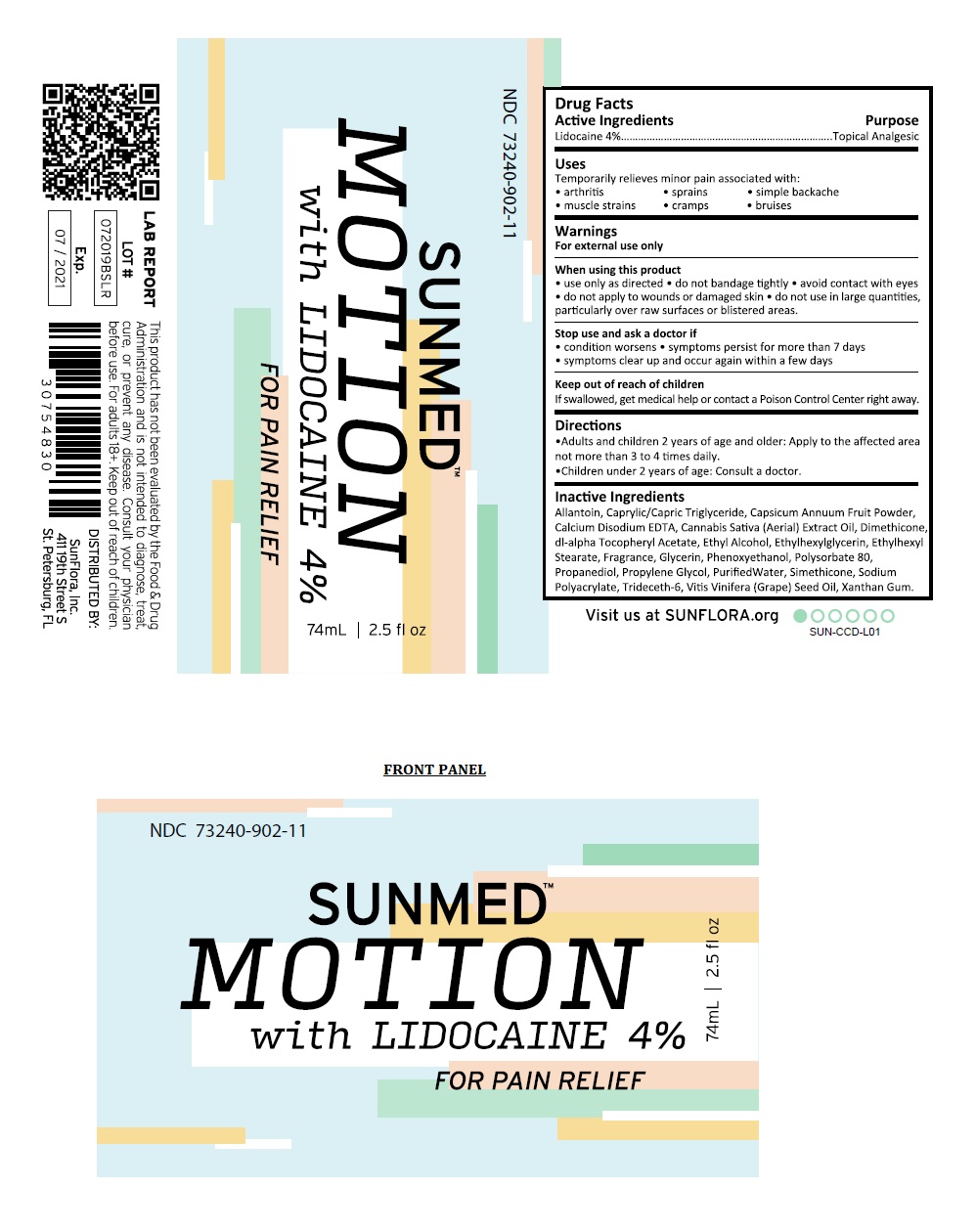 DRUG LABEL: SUNMED MOTION
NDC: 73240-902 | Form: LIQUID
Manufacturer: Sunflora Inc
Category: otc | Type: HUMAN OTC DRUG LABEL
Date: 20190822

ACTIVE INGREDIENTS: LIDOCAINE 4 g/100 mL
INACTIVE INGREDIENTS: ALLANTOIN; MEDIUM-CHAIN TRIGLYCERIDES; PAPRIKA; EDETATE CALCIUM DISODIUM ANHYDROUS; CANNABIS SATIVA SUBSP. SATIVA FLOWERING TOP; DIMETHICONE; .ALPHA.-TOCOPHEROL ACETATE, DL-; ALCOHOL; ETHYLHEXYLGLYCERIN; ETHYLHEXYL STEARATE; GLYCERIN; PHENOXYETHANOL; POLYSORBATE 80; PROPANEDIOL; PROPYLENE GLYCOL; WATER; SODIUM POLYACRYLATE (8000 MW); TRIDECETH-6; GRAPE SEED OIL; XANTHAN GUM

SUNMED MOTION

Active Ingredients

Lidocaine 4%

Purpose

Topical Analgesic

Uses

Temporarily relieves minor pain associated with:

• arthritis • sprains • simple backache • muscle strains • cramps • bruises

Warnings

For external use only

When using this product

• use only as directed • do not bandage tightly • avoid contact with eyes • do not apply to wounds or damaged skin • do not use in large quantities, particularly over raw surfaces or blistered areas.

Stop use and ask a doctor if

• condition worsens • symptoms persist for more than 7 days • symptoms clear up and occur again within a few days

Keep out of reach of children

If swallowed, get medical help or contact a Poison Control Center right away.

Directions

• Adults and children 2 years of age and older: Apply to the affected area not more than 3 to 4 times daily.

• Children under 2 years of age: Consult a doctor.

Inactive Ingredients

Allantoin, Caprylic/Capric Triglyceride, Capsicum Annuum Fruit Powder, Calcium Disodium EDTA, Cannabis Sativa (Aerial) Extract Oil, Dimethicone, dl-alpha Tocopheryl Acetate, Ethyl Alcohol, Ethylhexylglycerin, Ethylhexyl Stearate, Fragrance, Glycerin, Phenoxyethanol, Polysorbate 80, Propanediol, Propylene Glycol, Purified Water, Simethicone, Sodium Polyacrylate, Trideceth-6, Vitis Vinifera (Grape) Seed Oil, Xanthan Gum.

Visit us at SUNFLORA.org

This product has not been evaluated by the Food & Drug Administration and is not intended to diagnose, treat, cure, or prevent any disease. Consult your physician before use. For adults 18+.

DISTRIBUTED BY:

SunFlora, Inc.
411 19th street S

St. Petersberg, FL